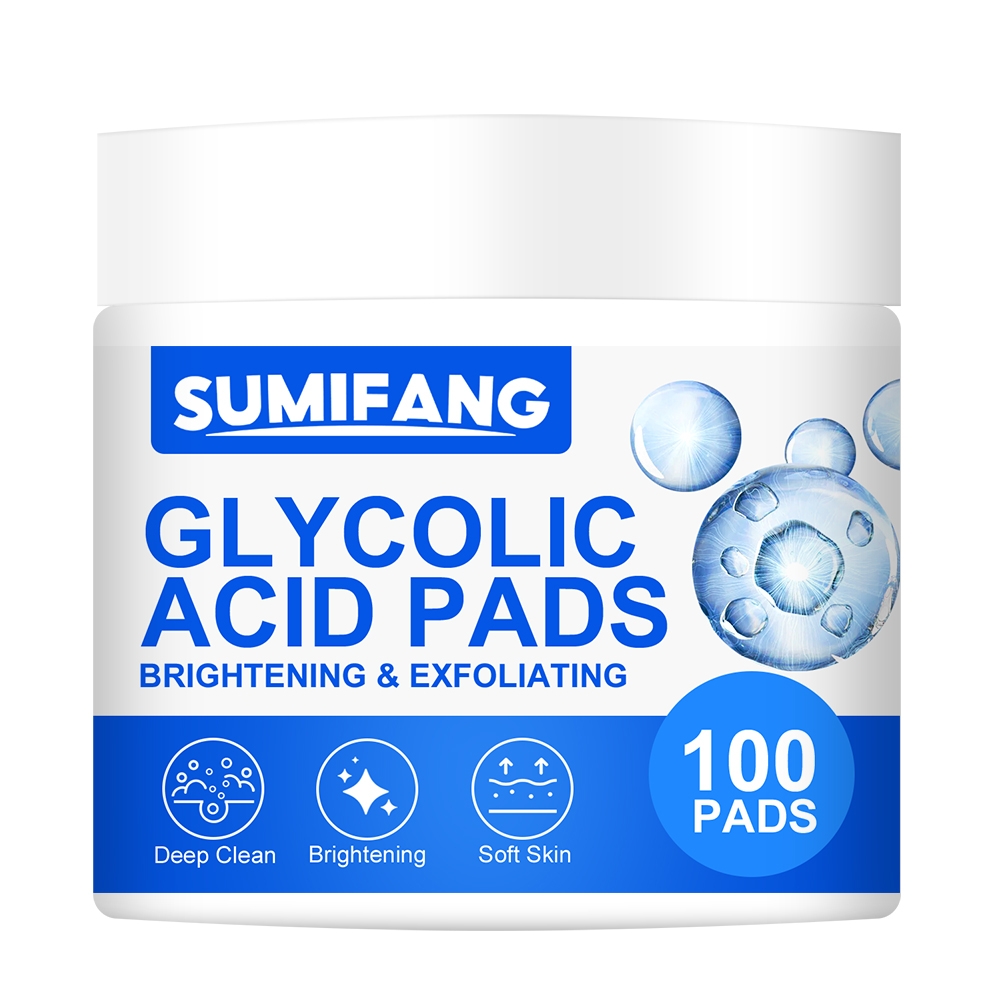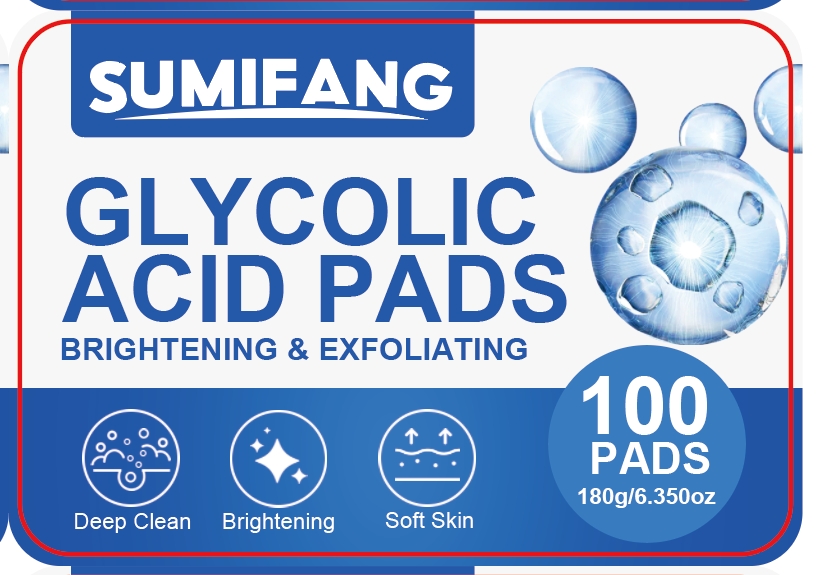 DRUG LABEL: GLYCOLIC ACID PADS
NDC: 84025-162 | Form: DRESSING
Manufacturer: Guangzhou Yanxi Biotechnology Co.. Ltd
Category: otc | Type: HUMAN OTC DRUG LABEL
Date: 20240819

ACTIVE INGREDIENTS: ASCORBIC ACID 3 mg/180 g; KOJIC ACID 5 mg/180 g
INACTIVE INGREDIENTS: WATER

DOSAGE AND ADMINISTRATION

Pads for deep cleansing of facial skin

WARNINGS

Keep out of children

INACTIVE INGREDIENT

AQUA

INDICATIONS AND USAGE

For facial skin care

Keep out of children

PURPOSE

Effectively cleans facial skin and keeps it dry and non-greasy